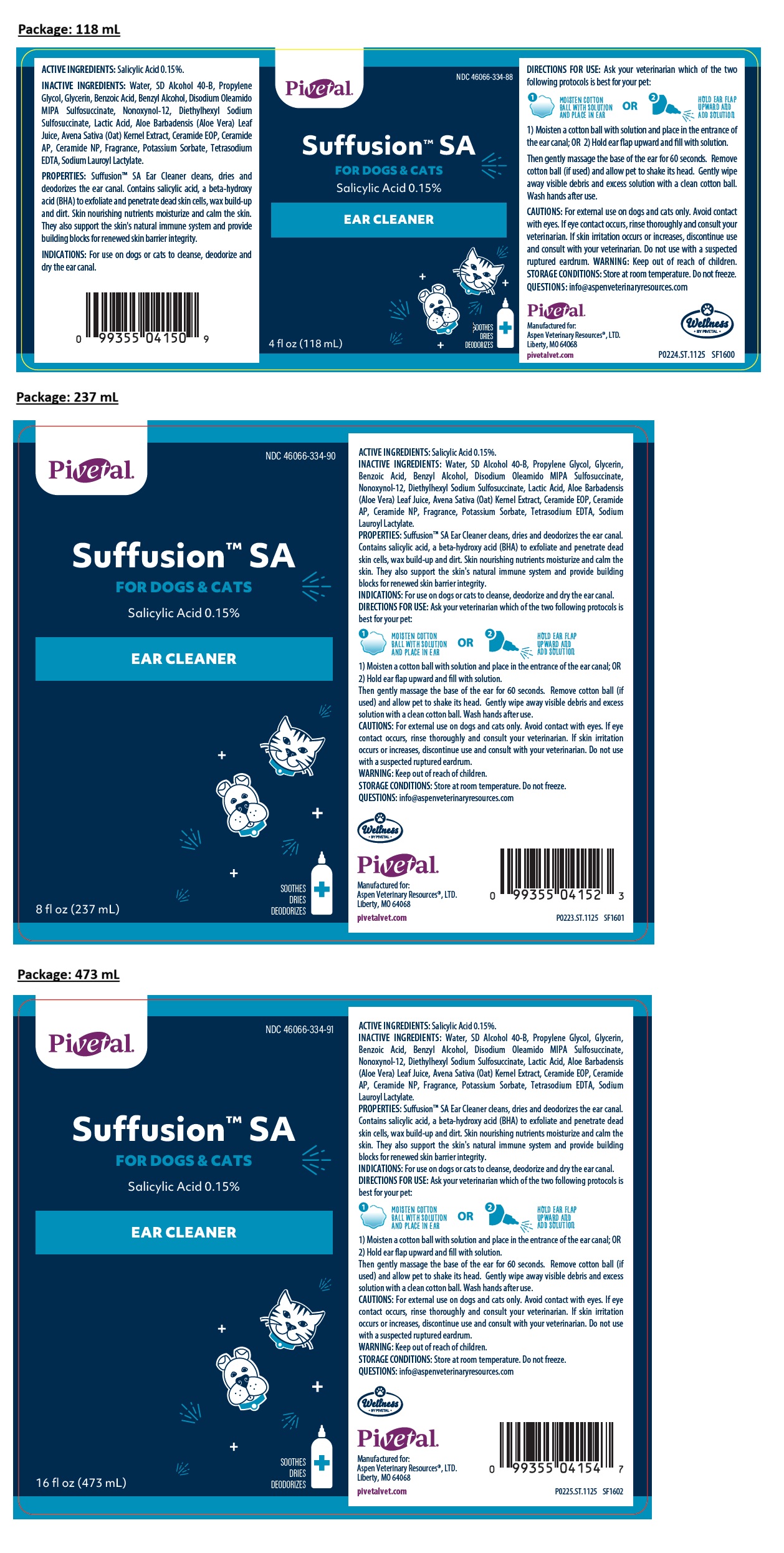 DRUG LABEL: Suffusion SA - FOR DOGS AND CATS - EAR CLEANER
NDC: 46066-334 | Form: SOLUTION
Manufacturer: Aspen Veterinary Resources, LTD.
Category: animal | Type: OTC ANIMAL DRUG LABEL
Date: 20251212

ACTIVE INGREDIENTS: SALICYLIC ACID 0.15 g/100 mL
INACTIVE INGREDIENTS: WATER; ALCOHOL; PROPYLENE GLYCOL; GLYCERIN; BENZOIC ACID; BENZYL ALCOHOL; DISODIUM OLEAMIDO MIPA-SULFOSUCCINATE; NONOXYNOL-12; DOCUSATE SODIUM; LACTIC ACID, UNSPECIFIED FORM; ALOE VERA LEAF JUICE; OAT; CERAMIDE 9; CERAMIDE AP; CERAMIDE NP; POTASSIUM SORBATE; EDETATE SODIUM; SODIUM LAUROYL LACTYLATE

Pivetal® Suffusion™ SA FOR DOGS & CATS EAR CLEANER

ACTIVE INGREDIENTS:

Salicylic Acid 0.15%.

INACTIVE INGREDIENTS:

Water, SD Alcohol 40-B, Propylene Glycol, Glycerin, Benzoic Acid, Benzyl Alcohol, Disodium Oleamido MIPA Sulfosuccinate, Nonoxynol-12, Diethylhexyl Sodium Sulfosuccinate, Lactic Acid, Aloe Barbadensis (Aloe Vera) Leaf Juice, Avena Sativa (Oat) Kernel Extract, Ceramide EOP, Ceramide AP, Ceramide NP, Fragrance, Potassium Sorbate, Tetrasodium EDTA, Sodium Lauroyl Lactylate.

PROPERTIES: Suffusion™ SA Ear Cleaner cleans, dries and deodorizes the ear canal. Contains salicylic acid, a beta-hydroxy acid (BHA) to exfoliate and penetrate dead skin cells, wax build-up and dirt. Skin nourishing nutrients moisturize and calm the skin. They also support the skin's natural immune system and provide building blocks for renewed skin barrier integrity.

INDICATIONS:

For use on dogs or cats to cleanse, deodorize and dry the ear canal.

DIRECTIONS FOR USE:

Ask your veterinarian which of the two following protocols is best for your pet:
1) MOISTEN COTTON BALL WITH SOLUTION AND PLACE IN EAR
OR
2) HOLD EAR FLAP UPWARD AND ADD SOLUTION

1. Moisten a cotton ball with solution and place in the entrance of the ear canal; OR 2) Hold ear flap upward and fill with solution.

Then gently massage the base of the ear for 60 seconds. Remove cotton ball (if used) and allow pet to shake its head. Gently wipe away visible debris and excess solution with a clean cotton ball. Wash hands after use.

CAUTIONS:

For external use on dogs and cats only. Avoid contact with eyes. If eye contact occurs, rinse thoroughly and consult your veterinarian. If skin irritation occurs or increases, discontinue use and consult with your veterinarian. Do not use with a suspected ruptured eardrum.

WARNING: Keep out of reach of children.

STORAGE CONDITIONS:

Store at room temperature. Do not freeze.

QUESTIONS:

info@aspenveterinaryresources.com

SOOTHES
DRIES
DEODORIZES

Manufactured for:
Aspen Veterinary Resources®, LTD.
Liberty, MO 64068
pivetalvet.com
Wellness
BY PIVETAL